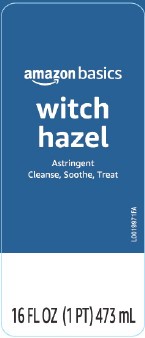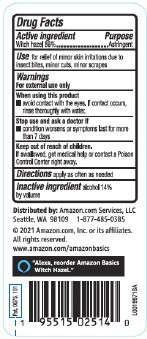 DRUG LABEL: Witch Hazel
NDC: 72288-922 | Form: LIQUID
Manufacturer: Amazon.Com Services LLC
Category: otc | Type: HUMAN OTC DRUG LABEL
Date: 20250519

ACTIVE INGREDIENTS: WITCH HAZEL 860 mg/1 mL
INACTIVE INGREDIENTS: ALCOHOL

Basics 822.001/822AA
Witch Hazel USP

Active Ingredient

Witch hazel 86%

Purpose

Astringent

Use

for relief of minor skin irritations due to insect bites, minor cuts, minor scrapes

Warnings

For external use only

When using this product

- avoid contact with the eyes. If contact occurs, rinse thoroughly with water.

Stop use and ask a doctor if

- condition worsens or symptoms persists for more than 7 days

Keep out of reach of children.

If swallowed, get medical help or contact a Poison Control Center right away.

Directions

apply as often as needed

Inactive ingredient

alcohol 14% by volume

Adverse reactons

DISTRIBUTED BY: Amazon.com, Services, LLC

Seattle, WA 98109 1-877-485-0385

©2021 Amazon.com, Inc. or its affiliates.

All rights reserved.

www. amazon.com/amazonbasics

"Alexa, reorder Amazon Basics Witch Hazel."

Pat. D675,101

Principal display panel

amazon basics

witch hazel

Astringent

Cleanse, Soothe, Treat

16 FL OZ (1 PT) 473 mL